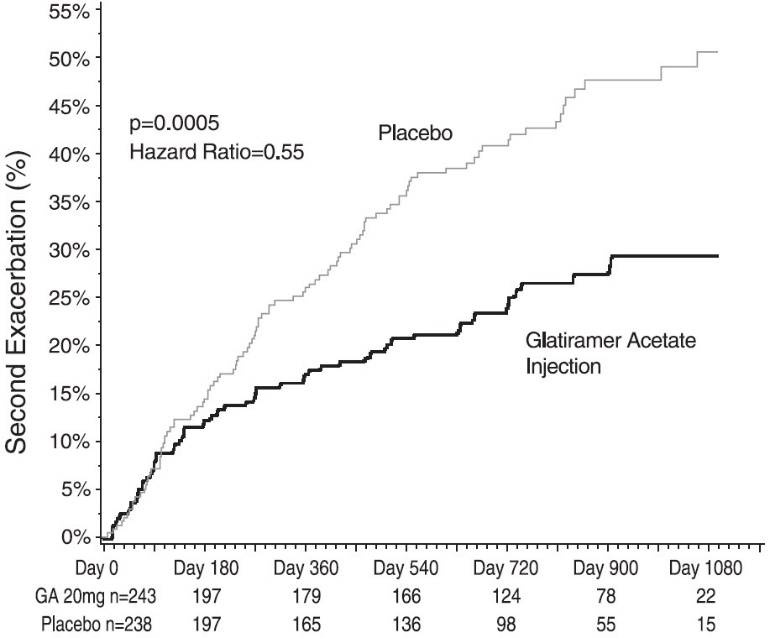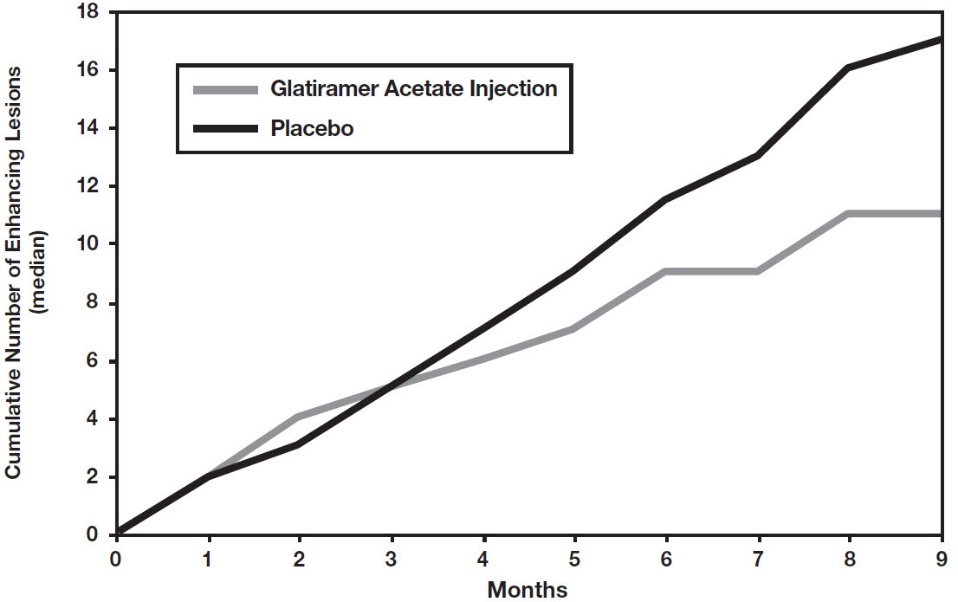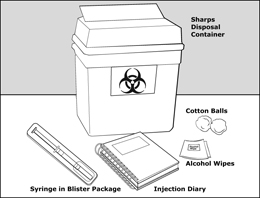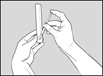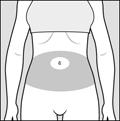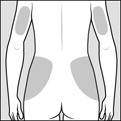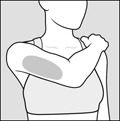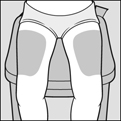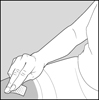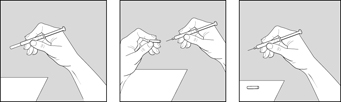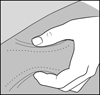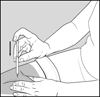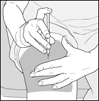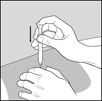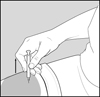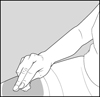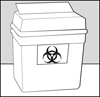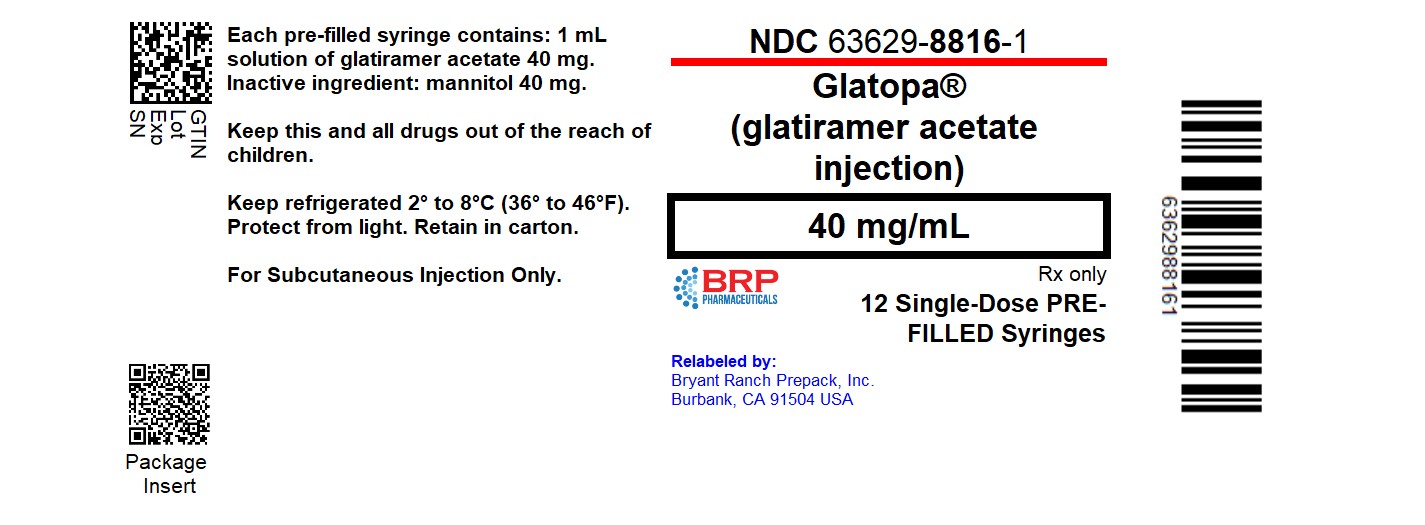 DRUG LABEL: Glatopa
NDC: 63629-8816 | Form: INJECTION, SOLUTION
Manufacturer: Bryant Ranch Prepack
Category: prescription | Type: HUMAN PRESCRIPTION DRUG LABEL
Date: 20250327

ACTIVE INGREDIENTS: GLATIRAMER ACETATE 40 mg/1 mL
INACTIVE INGREDIENTS: MANNITOL

HIGHLIGHTS OF PRESCRIBING INFORMATION

These highlights do not include all the information needed to use GLATOPA® safely and effectively. See full prescribing information for GLATOPA.
GLATOPA (glatiramer acetate injection), for subcutaneous use
Initial U.S. Approval: 1996

RECENT MAJOR CHANGES

Indications and Usage (1) 07/2019

Warnings and Precautions, Hepatic Injury (5.5) 07/2020

1 INDICATIONS AND USAGE

Glatopa is indicated for the treatment of relapsing-forms of multiple sclerosis (MS), to include clinically isolated syndrome, relapsing-remitting disease, and active secondary progressive disease, in adults (1).

2 DOSAGE AND ADMINISTRATION

- For subcutaneous injection only; doses are not interchangeable (2.1)
- Glatopa 20 mg/mL per day (2.1)
- Glatopa 40 mg/mL three times per week (2.1)
- Before use, allow the solution to warm to room temperature (2.2)

3 DOSAGE FORMS AND STRENGTHS

- Injection: 20 mg per mL in a single-dose, pre-filled syringe with a white plunger. (3)
- Injection: 40 mg per mL in a single-dose, pre-filled syringe with a blue plunger. (3)

4 CONTRAINDICATIONS

Known hypersensitivity to glatiramer acetate or mannitol (4)

5 WARNINGS AND PRECAUTIONS

- Immediate Post-Injection Reaction (flushing, chest pain, palpitations, tachycardia, anxiety, dyspnea, throat constriction, and/or urticaria), may occur within seconds to minutes after injection and are generally transient and self-limiting (5.1)
- Chest pain, usually transient (5.2)
- Lipoatrophy and skin necrosis may occur. Instruct patients in proper injection technique and to rotate injection sites (5.3)
- Glatopa can modify immune response (5.4)
- Hepatic Injury: if signs or symptoms of hepatic dysfunction occur, consider discontinuing Glatopa (5.5)

6 ADVERSE REACTIONS

- In controlled studies of glatiramer acetate injection 20 mg/mL, most common adverse reactions (≥10% and ≥1.5 times higher than placebo) were: injection site reactions, vasodilatation, rash, dyspnea, and chest pain (6.1)
- In a controlled study of glatiramer acetate injection 40 mg/mL, most common adverse reactions (≥10% and ≥1.5 times higher than placebo) were: injection site reactions (6.1)

To report SUSPECTED ADVERSE REACTIONS, contact Sandoz Inc. at 1-800-525-8747 or FDA at 1-800-FDA-1088 or www.fda.gov/medwatch.

FULL PRESCRIBING INFORMATION

1 INDICATIONS AND USAGE

Glatopa is indicated for the treatment of relapsing forms of multiple sclerosis (MS), to include clinically isolated syndrome, relapsing-remitting disease, and active secondary progressive disease, in adults.

2 DOSAGE AND ADMINISTRATION

2.1 Recommended Dose

Glatopa is for subcutaneous use only. Do not administer intravenously. The dosing schedule depends on the product strength that is selected. The recommended doses are:

- Glatopa 20 mg per mL: administer once per day

or

- Glatopa 40 mg per mL: administer three times per week and at least 48 hours apart.

Glatopa 20 mg per mL and Glatopa 40 mg per mL are not interchangeable.

2.2 Instructions for Use

Remove one blister-packaged pre-filled syringe from the refrigerated carton. Let the pre-filled syringe stand at room temperature for 20 minutes to allow the solution to warm to room temperature. Visually inspect the syringe for particulate matter and discoloration prior to administration. The solution in the syringe should appear clear, colorless to slightly yellow. If particulate matter or discoloration is observed, discard the syringe.

Areas for subcutaneous self-injection include arms, abdomen, hips, and thighs. The pre-filled syringe is for single use only. Discard unused portions.

3 DOSAGE FORMS AND STRENGTHS

- Injection: 20 mg per mL in a single-dose, pre-filled syringe with a white plunger. For subcutaneous use only.
- Injection: 40 mg per mL in a single-dose, pre-filled syringe with a blue plunger. For subcutaneous use only.

4 CONTRAINDICATIONS

Glatopa is contraindicated in patients with known hypersensitivity to glatiramer acetate or mannitol.

5 WARNINGS AND PRECAUTIONS

5.1 Immediate Post-Injection Reaction

Approximately 16% of patients exposed to glatiramer acetate injection 20 mg per mL in the five placebo-controlled trials compared to 4% of those on placebo, and approximately 2% of patients exposed to glatiramer acetate injection 40 mg per mL in a placebo-controlled trial compared to none on placebo, experienced a constellation of symptoms that may occur immediately (within seconds to minutes, with the majority of symptoms observed within 1 hour) after injection and included at least two of the following: flushing, chest pain, palpitations, tachycardia, anxiety, dyspnea, constriction of the throat, and urticaria. In general, these symptoms have their onset several months after the initiation of treatment, although they may occur earlier, and a given patient may experience one or several episodes of these symptoms. Whether or not any of these symptoms actually represent a specific syndrome is uncertain. Typically, the symptoms were transient and self-limited and did not require treatment; however, there have been reports of patients with similar symptoms who received emergency medical care. Whether an immunologic or nonimmunologic mechanism mediates these episodes, or whether several similar episodes seen in a given patient have identical mechanisms, is unknown.

5.2 Chest Pain

Approximately 13% of glatiramer acetate injection 20 mg per mL patients in the five placebo-controlled studies compared to 6% of placebo patients, and approximately 2% of patients exposed to glatiramer acetate injection 40 mg per mL in a placebo-controlled trial compared to 1% of placebo patients, experienced at least one episode of transient chest pain. While some of these episodes occurred in the context of the Immediate Post-Injection Reaction described above, many did not. The temporal relationship of this chest pain to an injection was not always known. The pain was usually transient, often unassociated with other symptoms, and appeared to have no clinical sequelae. Some patients experienced more than one such episode, and episodes usually began at least 1 month after the initiation of treatment. The pathogenesis of this symptom is unknown.

5.3 Lipoatrophy and Skin Necrosis

At injection sites, localized lipoatrophy and, rarely, injection site skin necrosis may occur. Lipoatrophy occurred in approximately 2% of patients exposed to glatiramer acetate injection 20 mg per mL in the five placebo-controlled trials compared to none on placebo, and 0.5% of patients exposed to glatiramer acetate injection 40 mg per mL in a single placebo-controlled trial and none on placebo. Skin necrosis has only been observed in the post-marketing setting. Lipoatrophy may occur at various times after treatment onset (sometimes after several months) and is thought to be permanent. There is no known therapy for lipoatrophy. To assist in possibly minimizing these events, the patient should be advised to follow proper injection technique and to rotate injection sites with each injection.

5.4 Potential Effects on Immune Response

Because glatiramer acetate injection can modify immune response, it may interfere with immune functions. For example, treatment with glatiramer acetate injection may interfere with the recognition of foreign antigens in a way that would undermine the body’s tumor surveillance and its defenses against infection. There is no evidence that glatiramer acetate injection does this, but there has not been a systematic evaluation of this risk. Because glatiramer acetate injection is an antigenic material, it is possible that its use may lead to the induction of host responses that are untoward, but systematic surveillance for these effects has not been undertaken.

Although glatiramer acetate injection is intended to minimize the autoimmune response to myelin, there is the possibility that continued alteration of cellular immunity due to chronic treatment with glatiramer acetate injection may result in untoward effects.

Glatiramer acetate-reactive antibodies are formed in most patients receiving glatiramer acetate. Studies in both the rat and monkey have suggested that immune complexes are deposited in the renal glomeruli. Furthermore, in a controlled trial of 125 RRMS patients given glatiramer acetate injection 20 mg per mL, subcutaneously every day for 2 years, serum IgG levels reached at least 3 times baseline values in 80% of patients by 3 months of initiation of treatment. By 12 months of treatment, however, 30% of patients still had IgG levels at least 3 times baseline values, and 90% had levels above baseline by 12 months. The antibodies are exclusively of the IgG subtype and predominantly of the IgG-1 subtype. No IgE type antibodies could be detected in any of the 94 sera tested; nevertheless, anaphylaxis can be associated with the administration of most any foreign substance, and therefore, this risk cannot be excluded.

5.5 Hepatic Injury

Cases of hepatic injury, some severe, including liver failure and hepatitis with jaundice, have been reported with Glatopa. Hepatic injury has occurred from days to years after initiating treatment with Glatopa. If signs or symptoms of liver dysfunction occur, consider discontinuation of Glatopa.

6 ADVERSE REACTIONS

The following serious adverse reactions are described elsewhere in the labeling:

- Immediate Post-Injection Reaction [see Warnings and Precautions (5.1)]
- Chest Pain [see Warnings and Precautions (5.2)]
- Lipoatrophy and Skin Necrosis [see Warnings and Precautions (5.3)]
- Potential Effects on Immune Response [see Warnings and Precautions (5.4)]
- Hepatic Injury [see Warnings and Precautions (5.5)]

6.1 Clinical Trials Experience

Because clinical trials are conducted under widely varying conditions, adverse reaction rates observed in the clinical trials of a drug cannot be directly compared to rates in the clinical trials of another drug and may not reflect the rates observed in practice.

Incidence in Controlled Clinical Trials

Glatiramer Acetate Injection 20 mg per mL per day

Among 563 patients treated with glatiramer acetate injection in blinded placebo-controlled trials, approximately 5% of the subjects discontinued treatment because of an adverse reaction. The adverse reactions most commonly associated with discontinuation were: injection site reactions, dyspnea, urticaria, vasodilatation, and hypersensitivity. The most common adverse reactions were: injection site reactions, vasodilatation, rash, dyspnea, and chest pain.

Table 1 lists signs and symptoms that occurred in at least 2% of patients treated with glatiramer acetate injection 20 mg per mL in the placebo-controlled trials. These signs and symptoms were numerically more common in patients treated with glatiramer acetate injection than in patients treated with placebo. Adverse reactions were usually mild in intensity.

Table 1: Adverse Reactions in Controlled Clinical Trials with an Incidence ≥2% of Patients and more frequent with Glatiramer Acetate Injection (20 mg per mL daily) than with Placebo

 |  | Glatiramer Acetate Injection 20 mg/mL (n=563) % | Placebo (n=564) %
Blood And Lymphatic System Disorders | Lymphadenopathy | 7 | 3
Cardiac Disorders | Palpitations | 9 | 4
 | Tachycardia | 5 | 2
Eye Disorders | Eye Disorder | 3 | 1
 | Diplopia | 3 | 2
Gastrointestinal Disorders | Nausea | 15 | 11
 | Vomiting | 7 | 4
 | Dysphagia | 2 | 1
General Disorders And Administration | Injection Site Erythema | 43 | 10
Site Conditions | Injection Site Pain | 40 | 20
 | Injection Site Pruritus | 27 | 4
 | Injection Site Mass | 26 | 6
 | Asthenia | 22 | 21
 | Pain | 20 | 17
 | Injection Site Edema | 19 | 4
 | Chest Pain | 13 | 6
 | Injection Site Inflammation | 9 | 1
 | Edema | 8 | 2
 | Injection Site Reaction | 8 | 1
 | Pyrexia | 6 | 5
 | Injection Site Hypersensitivity | 4 | 0
 | Local Reaction | 3 | 1
 | Chills | 3 | 1
 | Face Edema | 3 | 1
 | Edema Peripheral | 3 | 2
 | Injection Site Fibrosis | 2 | 1
 | Injection Site Atrophy [Injection site atrophy comprises terms relating to localized lipoatrophy at injection site] | 2 | 0
Immune System Disorders | Hypersensitivity | 3 | 2
Infections And Infestations | Infection | 30 | 28
 | Influenza | 14 | 13
 | Rhinitis | 7 | 5
 | Bronchitis | 6 | 5
 | Gastroenteritis | 6 | 4
 | Vaginal Candidiasis | 4 | 2
Metabolism And Nutrition Disorders | Weight Increased | 3 | 1
Musculoskeletal And Connective | Back Pain | 12 | 10
Tissue Disorders
Neoplasms Benign, Malignant And | Benign Neoplasm of Skin | 2 | 1
Unspecified (Incl Cysts And Polyps)
Nervous System Disorders | Tremor | 4 | 2
 | Migraine | 4 | 2
 | Syncope | 3 | 2
 | Speech Disorder | 2 | 1
Psychiatric Disorders | Anxiety | 13 | 10
 | Nervousness | 2 | 1
Renal And Urinary Disorders | Micturition Urgency | 5 | 4
Respiratory, Thoracic And Mediastinal | Dyspnea | 14 | 4
Disorders | Cough | 6 | 5
 | Laryngospasm | 2 | 1
Skin And Subcutaneous Tissue | Rash | 19 | 11
Disorders | Hyperhidrosis | 7 | 5
 | Pruritus | 5 | 4
 | Urticaria | 3 | 1
 | Skin Disorder | 3 | 1
Vascular Disorders | Vasodilatation | 20 | 5

Adverse reactions which occurred only in 4 to 5 more subjects in the glatiramer acetate injection group than in the placebo group (less than 1% difference), but for which a relationship to glatiramer acetate injection could not be excluded, were arthralgia and herpes simplex.

Laboratory analyses were performed on all patients participating in the clinical program for glatiramer acetate injection. Clinically-significant laboratory values for hematology, chemistry, and urinalysis were similar for both glatiramer acetate injection and placebo groups in blinded clinical trials. In controlled trials one patient discontinued treatment due to thrombocytopenia (16 x 10^9/L), which resolved after discontinuation of treatment.

Data on adverse reactions occurring in the controlled clinical trials of glatiramer acetate injection 20 mg per mL were analyzed to evaluate differences based on sex. No clinically-significant differences were identified. Ninety-six percent of patients in these clinical trials were Caucasian. The majority of patients treated with glatiramer acetate injection were between the ages of 18 and 45. Consequently, data are inadequate to perform an analysis of the adverse reaction incidence related to clinically-relevant age subgroups.

Other Adverse Reactions

In the paragraphs that follow, the frequencies of less commonly reported adverse clinical reactions are presented. Because the reports include reactions observed in open and uncontrolled premarketing studies (n=979), the role of glatiramer acetate injection in their causation cannot be reliably determined. Furthermore, variability associated with adverse reaction reporting, the terminology used to describe adverse reactions, etc., limit the value of the quantitative frequency estimates provided. Reaction frequencies are calculated as the number of patients who used glatiramer acetate injection and reported a reaction divided by the total number of patients exposed to glatiramer acetate injection. All reported reactions are included except those already listed in the previous table, those too general to be informative, and those not reasonably associated with the use of the drug. Reactions are further classified within body system categories and enumerated in order of decreasing frequency using the following definitions: Frequent adverse reactions are defined as those occurring in at least 1/100 patients and infrequent adverse reactions are those occurring in 1/100 to 1/1,000 patients.

Body as a Whole

Frequent: Abscess.

Infrequent: Injection site hematoma, moon face, cellulitis, hernia, injection site abscess, serum sickness, suicide attempt, injection site hypertrophy, injection site melanosis, lipoma, and photosensitivity reaction.

Cardiovascular

Frequent: Hypertension.

Infrequent: Hypotension, midsystolic click, systolic murmur, atrial fibrillation, bradycardia, fourth heart sound, postural hypotension, and varicose veins.

Digestive

Infrequent: Dry mouth, stomatitis, burning sensation on tongue, cholecystitis, colitis, esophageal ulcer, esophagitis, gastrointestinal carcinoma, gum hemorrhage, hepatomegaly, increased appetite, melena, mouth ulceration, pancreas disorder, pancreatitis, rectal hemorrhage, tenesmus, tongue discoloration, and duodenal ulcer.

Endocrine

Infrequent: Goiter, hyperthyroidism, and hypothyroidism.

Gastrointestinal

Frequent: Bowel urgency, oral moniliasis, salivary gland enlargement, tooth caries, and ulcerative stomatitis.

Hemic and Lymphatic

Infrequent: Leukopenia, anemia, cyanosis, eosinophilia, hematemesis, lymphedema, pancytopenia, and splenomegaly.

Metabolic and Nutritional

Infrequent: Weight loss, alcohol intolerance, Cushing’s syndrome, gout, abnormal healing, and xanthoma.

Musculoskeletal

Infrequent: Arthritis, muscle atrophy, bone pain, bursitis, kidney pain, muscle disorder, myopathy, osteomyelitis, tendon pain, and tenosynovitis.

Nervous

Frequent: Abnormal dreams, emotional lability, and stupor.

Infrequent: Aphasia, ataxia, convulsion, circumoral paresthesia, depersonalization, hallucinations, hostility, hypokinesia, coma, concentration disorder, facial paralysis, decreased libido, manic reaction, memory impairment, myoclonus, neuralgia, paranoid reaction, paraplegia, psychotic depression, and transient stupor.

Respiratory

Frequent: Hyperventilation and hay fever.

Infrequent: Asthma, pneumonia, epistaxis, hypoventilation, and voice alteration.

Skin and Appendages

Frequent: Eczema, herpes zoster, pustular rash, skin atrophy, and warts.

Infrequent: Dry skin, skin hypertrophy, dermatitis, furunculosis, psoriasis, angioedema, contact dermatitis, erythema nodosum, fungal dermatitis, maculopapular rash, pigmentation, benign skin neoplasm, skin carcinoma, skin striae, and vesiculobullous rash.

Special Senses

Frequent: Visual field defect.

Infrequent: Dry eyes, otitis externa, ptosis, cataract, corneal ulcer, mydriasis, optic neuritis, photophobia, and taste loss.

Urogenital

Frequent: Amenorrhea, hematuria, impotence, menorrhagia, suspicious papanicolaou smear, urinary frequency, and vaginal hemorrhage.

Infrequent: Vaginitis, flank pain (kidney), abortion, breast engorgement, breast enlargement, carcinoma in situ cervix, fibrocystic breast, kidney calculus, nocturia, ovarian cyst, priapism, pyelonephritis, abnormal sexual function, and urethritis.

Glatiramer Acetate Injection 40 mg per mL three times per week

Among 943 patients treated with glatiramer acetate injection 40 mg per mL three times per week in a blinded, placebo-controlled trial, approximately 3% of the subjects discontinued treatment because of an adverse reaction. The most common adverse reactions were injection site reactions, which were also the most common cause of discontinuation.

Table 2 lists signs and symptoms that occurred in at least 2% of patients treated with glatiramer acetate injection 40 mg per mL in the blinded, placebo-controlled trial. These signs and symptoms were numerically more common in patients treated with glatiramer acetate injection 40 mg per mL than in patients treated with placebo. Adverse reactions were usually mild in intensity.

Table 2: Adverse Reactions in a Controlled Clinical Trial with an Incidence ≥2% of Patients and more frequent with Glatiramer Acetate Injection (40 mg per mL three times per week) than with Placebo

 |  | Glatiramer Acetate Injection 40 mg/mL (n=943) % | Placebo (n=461) %
General Disorders And Administration Site Conditions | Injection Site Erythema | 22 | 2
General Disorders And Administration Site Conditions | Injection Site Pain | 10 | 2
General Disorders And Administration Site Conditions | Injection Site Mass | 6 | 0
General Disorders And Administration Site Conditions | Injection Site Pruritus | 6 | 0
General Disorders And Administration Site Conditions | Injection Site Edema | 6 | 0
General Disorders And Administration Site Conditions | Pyrexia | 3 | 2
General Disorders And Administration Site Conditions | Influenza-like Illness | 3 | 2
General Disorders And Administration Site Conditions | Injection Site Inflammation | 2 | 0
General Disorders And Administration Site Conditions | Chills | 2 | 0
General Disorders And Administration Site Conditions | Chest Pain | 2 | 1
Infections And Infestations | Nasopharyngitis | 11 | 9
Infections And Infestations | Respiratory Tract Infection Viral | 3 | 2
Respiratory, Thoracic and Mediastinal Disorders | Dyspnea | 3 | 0
Vascular Disorders | Vasodilatation | 3 | 0
Gastrointestinal Disorders | Nausea | 2 | 1
Skin And Subcutaneous Tissue Disorders | Erythema | 2 | 0
Skin And Subcutaneous Tissue Disorders | Rash | 2 | 1

No new adverse reactions appeared in subjects treated with glatiramer acetate injection 40 mg per mL three times per week as compared to subjects treated with glatiramer acetate injection 20 mg per mL per day in clinical trials and during postmarketing experience. Data on adverse reactions occurring in the controlled clinical trial of glatiramer acetate injection 40 mg per mL were analyzed to evaluate differences based on sex. No clinically significant differences were identified. Ninety-eight percent of patients in this clinical trial were Caucasian and the majority were between the ages of 18 and 50. Consequently, data are inadequate to perform an analysis of the adverse reaction incidence related to clinically-relevant age groups.

6.2 Postmarketing Experience

The following adverse reactions have been identified during postapproval use of glatiramer acetate injection. Because these reactions are reported voluntarily from a population of uncertain size, it is not always possible to reliably estimate their frequency or establish a causal relationship to drug exposure.

Body as a Whole: sepsis; SLE syndrome; hydrocephalus; enlarged abdomen; allergic reaction; anaphylactoid reaction

Cardiovascular System: thrombosis; peripheral vascular disease; pericardial effusion; myocardial infarct; deep thrombophlebitis; coronary occlusion; congestive heart failure; cardiomyopathy; cardiomegaly; arrhythmia; angina pectoris

Digestive System: tongue edema; stomach ulcer; hemorrhage; eructation

Hemic and Lymphatic System: thrombocytopenia; lymphoma-like reaction; acute leukemia

Hepatobiliary Disorders: cholelithiasis; liver function abnormality; cirrhosis of the liver; hepatitis; hepatic injury [see Warnings and Precautions (5.5)]

Metabolic and Nutritional Disorders: hypercholesterolemia

Musculoskeletal System: rheumatoid arthritis; generalized spasm

Nervous System: myelitis; meningitis; CNS neoplasm; cerebrovascular accident; brain edema; abnormal dreams; aphasia; convulsion; neuralgia

Respiratory System: pulmonary embolus; pleural effusion; carcinoma of lung

Special Senses: glaucoma; blindness

Urogenital System: urogenital neoplasm; urine abnormality; ovarian carcinoma; nephrosis; kidney failure; breast carcinoma; bladder carcinoma; urinary frequency

7 DRUG INTERACTIONS

Interactions between glatiramer acetate injection and other drugs have not been fully evaluated. Results from existing clinical trials do not suggest any significant interactions of glatiramer acetate injection with therapies commonly used in MS patients, including the concurrent use of corticosteroids for up to 28 days. Glatiramer acetate injection has not been formally evaluated in combination with interferon beta.

8 USE IN SPECIFIC POPULATIONS

8.1 Pregnancy

Risk Summary

Available human data on the use of Glatopa in pregnant women are not sufficient to support conclusions about drug-associated risk for major birth defects and miscarriage. Administration of glatiramer acetate by subcutaneous injection to pregnant rats and rabbits resulted in no adverse effects on embryo-fetal or offspring development (see Data).

The estimated background risk of major birth defects and miscarriage for the indicated population is unknown. In the US general population, the estimated background risk of major birth defects and miscarriage in clinically recognized pregnancies is 2% to 4% and 15% to 20%, respectively.

Data

Human Data

There are no adequate and well-controlled studies of Glatopa in pregnant women. The available postmarketing reports, case series, and small cohort studies do not provide sufficient information to support conclusions about drug-associated risk for major birth defects and miscarriage.

Animal Data

In rats or rabbits receiving glatiramer acetate by subcutaneous injection during the period of organogenesis, no adverse effects on embryo-fetal development were observed at doses up to 37.5 mg/kg/day (18 and 36 times, respectively, the therapeutic human dose of 20 mg/day on a mg/m^2 basis). In rats receiving subcutaneous glatiramer acetate at doses of up to 36 mg/kg from day 15 of pregnancy throughout lactation, no significant effects on delivery or on offspring growth and development were observed.

8.2 Lactation

Risk Summary

There are no data on the presence of glatiramer acetate in human milk, the effects on breastfed infants, or the effects on milk production.

The developmental and health benefits of breastfeeding should be considered along with the mother’s clinical need for Glatopa and any potential adverse effects on the breastfed infant from Glatopa or from the underlying maternal condition.

8.4 Pediatric Use

The safety and effectiveness of Glatopa have not been established in patients under 18 years of age.

8.5 Geriatric Use

Glatopa has not been studied in elderly patients.

8.6 Use in Patients with Impaired Renal Function

The pharmacokinetics of glatiramer acetate in patients with impaired renal function have not been determined.

11 DESCRIPTION

Glatiramer acetate, the active ingredient of Glatopa, consists of the acetate salts of synthetic polypeptides, containing four naturally occurring amino acids: L-glutamic acid, L-alanine, L-tyrosine, and L-lysine with an average molar fraction of 0.141, 0.427, 0.095, and 0.338, respectively. The average molecular weight of glatiramer acetate is 5,000 – 9,000 daltons. Glatiramer acetate is identified by specific antibodies.

Chemically, glatiramer acetate is designated L-glutamic acid polymer with L-alanine, L-lysine and L-tyrosine, acetate (salt). Its structural formula is:

(Glu, Ala, Lys, Tyr)x•xCH3COOH

(C5H9NO4•C3H7NO2•C6H14N2O2•C9H11NO3)x•xC2H4O2

CAS - 147245-92-9

Glatopa is a clear, colorless to slightly yellow, sterile, nonpyrogenic solution for subcutaneous injection. Each 1 mL of glatiramer acetate solution contains 20 mg or 40 mg of glatiramer acetate and the following inactive ingredient: 40 mg of mannitol. The pH of the solutions is approximately 5.5 to 7.0. The biological activity of glatiramer acetate is determined by its ability to block the induction of experimental autoimmune encephalomyelitis (EAE) in mice.

12 CLINICAL PHARMACOLOGY

12.1 Mechanism of Action

The mechanism(s) by which glatiramer acetate exerts its effects in patients with MS are not fully understood. However, glatiramer acetate is thought to act by modifying immune processes that are believed to be responsible for the pathogenesis of MS. This hypothesis is supported by findings of studies that have been carried out to explore the pathogenesis of experimental autoimmune encephalomyelitis, a condition induced in animals through immunization against central nervous system derived material containing myelin and often used as an experimental animal model of MS. Studies in animals and in vitro systems suggest that upon its administration, glatiramer acetate-specific suppressor T-cells are induced and activated in the periphery.

Because glatiramer acetate can modify immune functions, concerns exist about its potential to alter naturally-occurring immune responses. There is no evidence that glatiramer acetate does this, but this has not been systematically evaluated [see Warnings and Precautions (5.4)].

12.3 Pharmacokinetics

Results obtained in pharmacokinetic studies performed in humans (healthy volunteers) and animals support that a substantial fraction of the therapeutic dose delivered to patients subcutaneously is hydrolyzed locally. Larger fragments of glatiramer acetate can be recognized by glatiramer acetate-reactive antibodies. Some fraction of the injected material, either intact or partially hydrolyzed, is presumed to enter the lymphatic circulation, enabling it to reach regional lymph nodes, and some may enter the systemic circulation intact.

13 NONCLINICAL TOXICOLOGY

13.1 Carcinogenesis, Mutagenesis, Impairment of Fertility

Carcinogenesis

In a 2-year carcinogenicity study, mice were administered up to 60 mg/kg/day glatiramer acetate by subcutaneous injection (up to 15 times the human therapeutic dose of 20 mg/day on a mg/m^2 basis). No increase in systemic neoplasms was observed. In males receiving the 60-mg/kg/day dose, there was an increased incidence of fibrosarcomas at the injection sites. These sarcomas were associated with skin damage precipitated by repetitive injections of an irritant over a limited skin area.

In a 2-year carcinogenicity study, rats were administered up to 30 mg/kg/day glatiramer acetate by subcutaneous injection (up to 15 times the human therapeutic dose on a mg/m^2 basis). No increase in neoplasms was observed.

Mutagenesis

Glatiramer acetate was not mutagenic in in vitro (Ames test, mouse lymphoma tk) assays. Glatiramer acetate was clastogenic in two separate in vitro chromosomal aberration assays in cultured human lymphocytes but not clastogenic in an in vivo mouse bone marrow micronucleus assay.

Impairment of Fertility

When glatiramer acetate was administered by subcutaneous injection prior to and during mating (males and females) and throughout gestation and lactation (females) at doses up to 36 mg/kg/day (18 times the human therapeutic dose on a mg/m^2 basis) no adverse effects were observed on reproductive or developmental parameters.

14 CLINICAL STUDIES

Evidence supporting the effectiveness of glatiramer acetate injection derives from five placebo-controlled trials, four of which used a glatiramer acetate injection dose of 20 mg per mL per day and one of which used a glatiramer acetate injection dose of 40 mg per mL three times per week.

Glatiramer acetate injection 20 mg per mL per day

Study 1 was performed at a single center. Fifty patients were enrolled and randomized to receive daily doses of either glatiramer acetate injection, 20 mg per mL subcutaneously, or placebo (glatiramer acetate injection: n=25; placebo: n=25). Patients were diagnosed with RRMS by standard criteria, and had at least 2 exacerbations during the 2 years immediately preceding enrollment. Patients were ambulatory, as evidenced by a score of no more than 6 on the Kurtzke Disability Scale Score (DSS), a standard scale ranging from 0–Normal to 10–Death due to MS. A score of 6 is defined as one at which a patient is still ambulatory with assistance; a score of 7 means the patient must use a wheelchair.

Patients were examined every 3 months for 2 years, as well as within several days of a presumed exacerbation. To confirm an exacerbation, a blinded neurologist had to document objective neurologic signs, as well as document the existence of other criteria (e.g., the persistence of the neurological signs for at least 48 hours).

The protocol-specified primary outcome measure was the proportion of patients in each treatment group who remained exacerbation free for the 2 years of the trial, but two other important outcomes were also specified as endpoints: the frequency of attacks during the trial, and the change in the number of attacks compared with the number which occurred during the previous 2 years.

Table 3 presents the values of the three outcomes described above, as well as several protocol-specified secondary measures. These values are based on the intent-to-treat population (i.e., all patients who received at least 1 dose of treatment and who had at least 1 on-treatment assessment):

Table 3: Study 1 Efficacy Results
 | Glatiramer Acetate Injection 20 mg/mL (n=25) | Placebo (n=25) | P-Value
% Relapse-Free Patients | 14/25 (56%) | 7/25 (28%) | 0.085
Mean Relapse Frequency | 0.6/2 years | 2.4/2 years | 0.005
Reduction in Relapse Rate Compared to Prestudy | 3.2 | 1.6 | 0.025
Median Time to First Relapse (days) | >700 | 150 | 0.03
% of Progression-Free [Progression was defined as an increase of at least 1 point on the DSS, persisting for at least 3 consecutive months.] Patients | 20/25 (80%) | 13/25 (52%) | 0.07

Study 2 was a multicenter trial of similar design which was performed in 11 US centers. A total of 251 patients (glatiramer acetate injection: n=125; placebo: n=126) were enrolled. The primary outcome measure was the Mean 2-Year Relapse Rate. Table 4 presents the values of this outcome for the intent-to-treat population, as well as several secondary measures:

Table 4: Study 2 Efficacy Results
 | Glatiramer Acetate Injection 20 mg/mL (n=125) | Placebo (n=126) | P-Value
Mean No. of Relapses | 1.19/2 years | 1.68/2 years | 0.055
% Relapse-Free Patients | 42/125 (34%) | 34/126 (27%) | 0.25
Median Time to First Relapse (days) | 287 | 198 | 0.23
% of Progression-Free Patients | 98/125 (78%) | 95/126 (75%) | 0.48
Mean Change in DSS | -0.05 | +0.21 | 0.023

In both studies, glatiramer acetate injection exhibited a clear beneficial effect on relapse rate, and it is based on this evidence that glatiramer acetate injection is considered effective.

In Study 3, 481 patients who had recently (within 90 days) experienced an isolated demyelinating event and who had lesions typical of multiple sclerosis on brain MRI were randomized to receive either glatiramer acetate injection 20 mg per mL (n=243) or placebo (n=238). The primary outcome measure was time to development of a second exacerbation. Patients were followed for up to three years or until they reached the primary endpoint. Secondary outcomes were brain MRI measures, including number of new T2 lesions and T2 lesion volume.

Time to development of a second exacerbation was significantly delayed in patients treated with glatiramer acetate injection compared to placebo (Hazard Ratio=0.55; 95% confidence interval 0.40 to 0.77; Figure 1). The Kaplan-Meier estimates of the percentage of patients developing a relapse within 36 months were 42.9% in the placebo group and 24.7% in the glatiramer acetate injection group.

Figure 1: Time to Second Exacerbation

Patients treated with glatiramer acetate injection demonstrated fewer new T2 lesions at the last observation (rate ratio 0.41; confidence interval 0.28 to 0.59; p<0.0001). Additionally, baseline-adjusted T2 lesion volume at the last observation was lower for patients treated with glatiramer acetate injection (ratio of 0.89; confidence interval 0.84 to 0.94; p=0.0001).

Study 4 was a multinational study in which MRI parameters were used both as primary and secondary endpoints. A total of 239 patients with RRMS (glatiramer acetate injection: n=119; and placebo: n=120) were randomized. Inclusion criteria were similar to those in the second study with the additional criterion that patients had to have at least one Gd-enhancing lesion on the screening MRI. The patients were treated in a double-blind manner for nine months, during which they underwent monthly MRI scanning. The primary endpoint for the double-blind phase was the total cumulative number of T1 Gd-enhancing lesions over the nine months. Table 5 summarizes the results for the primary outcome measure monitored during the trial for the intent-to-treat cohort.

Table 5: Study 4 MRI Results
 | Glatiramer Acetate Injection 20 mg/mL (n=119) | Placebo (n=120) | P-Value
Medians of the Cumulative Number of T1 Gd-Enhancing Lesions | 11 | 17 | 0.0030

Figure 2 displays the results of the primary outcome on a monthly basis.

Figure 2: Median Cumulative Number of Gd-Enhancing Lesions

Glatiramer Acetate Injection 40 mg per mL three times per week

Study 5 was a double-blind, placebo-controlled, multinational study with a total of 1404 patients with RRMS randomized in a 2:1 ratio to receive either glatiramer acetate injection 40 mg per mL (n=943) or placebo (n=461) three times a week for 12 months. Patients had a median of 2 relapses in the 2 years prior to screening and had not received any interferon-beta for at least 2 months prior to screening. Baseline EDSS scores ranged from 0 to 5.5 with a median of 2.5. Neurological evaluations were performed at baseline, every three months, and at unscheduled visits for suspected relapse or early termination. MRI was performed at baseline, months 6 and 12, or early termination. A total of 91% of those assigned to glatiramer acetate injection and 93% of those assigned to placebo completed treatment at 12 months.

The primary outcome measure was the total number of confirmed relapses (persistence of neurological symptoms for at least 48 hours confirmed on examination with objective signs). The effect of glatiramer acetate injection on several magnetic resonance imaging (MRI) variables, including number of new or enlarging T2 lesions and number of enhancing lesions on T1-weighted images, was also measured at months 6 and 12.

Table 6 presents the results for the intent-to-treat population.

Table 6: Study 5 Efficacy and MRI Results
 | Glatiramer Acetate Injection 40 mg/mL (n=943) | Placebo (n=461) | P-Value
Clinical Endpoints
Number of confirmed relapses during the 12-month placebo-controlled phase
Adjusted Mean Estimates Relative risk reduction | 0.331 34% | 0.505 | <0.0001
MRI Endpoints
Cumulative number of new or enlarging T2 lesions at Months 6 and 12
Adjusted Mean Estimates Relative risk reduction | 3.650 35% | 5.592 | <0.0001
Cumulative number of enhancing lesions on T1-weighted images at Months 6 and 12
Adjusted Mean Estimates Relative risk reduction | 0.905 45% | 1.639 | <0.0001

16 HOW SUPPLIED/STORAGE AND HANDLING

Glatopa (glatiramer acetate injection) is a clear, colorless to slightly yellow, sterile, nonpyrogenic solution in a 1 mL single-dose glass syringe with attached 1/2 inch length, 29 gauge needle supplied as:

- 40 mg per mL in a single-dose, pre-filled syringe with a blue plunger, in individual blister packages supplied in 12-count cartons (NDC: 63629-8816-1)

Store Glatopa refrigerated at 2°C to 8°C (36°F to 46°F). If needed, the patient may store Glatopa at room temperature, 15°C to 30°C (59°F to 86°F), for up to one month, but refrigeration is preferred. Avoid exposure to higher temperatures or intense light. Do not freeze Glatopa. If a Glatopa syringe freezes, it should be discarded.

Repackaged/Relabeled by:
Bryant Ranch Prepack, Inc.
Burbank, CA 91504

17 PATIENT COUNSELING INFORMATION

Advise the patient to read the FDA-approved patient labeling (Patient Information and Instructions for Use).

Immediate Post-Injection Reaction

Advise patients that Glatopa may cause various symptoms after injection, including flushing, chest pain, palpitations, tachycardia, anxiety, dyspnea, constriction of the throat, and urticaria. These symptoms occur within seconds to minutes after injection and are generally transient and self-limited and do not require specific treatment. Inform patients that these symptoms may occur early or may have their onset several months after the initiation of treatment. A patient may experience one or several episodes of these symptoms.

Chest Pain

Advise patients that they may experience transient chest pain either as part of the Immediate Post-Injection Reaction or in isolation. Inform patients that the pain should be transient. Some patients may experience more than one such episode, usually beginning at least one month after the initiation of treatment. Patients should be advised to seek medical attention if they experience chest pain of unusual duration or intensity.

Lipoatrophy and Skin Necrosis at Injection Site

Advise patients that localized lipoatrophy, and rarely, skin necrosis may occur at injection sites. Instruct patients to follow proper injection technique and to rotate injection areas and sites with each injection to minimize these risks.

Hepatic Injury

Advise patients that hepatic injury, including hepatic failure and hepatitis with jaundice, has been reported with the use of Glatopa. Educate patients about the signs and symptoms of hepatic injury and instruct patients to report them immediately to their healthcare provider [see Warning and Precautions (5.5)].

Pregnancy

Instruct patients that if they are pregnant or plan to become pregnant while taking Glatopa they should inform their physician [see Use in Specific Populations (8.1)].

Lactation

Advise patients to notify their healthcare provider if they are breastfeeding or intend to breastfeed during Glatopa therapy [see Use in Specific Populations (8.2)].

Instructions for Use

Instruct patients to read the Glatopa Patient Information leaflet carefully. Glatopa 20 mg per mL and Glatopa 40 mg per mL are not interchangeable. Glatiramer acetate injection 20 mg per mL is administered daily and glatiramer acetate injection 40 mg per mL is administered three times per week. Caution patients to use aseptic technique. The first injection should be performed under the supervision of a health care professional. Instruct patients to rotate injection areas and sites with each injection. Caution patients against the reuse of needles or syringes. Instruct patients in safe disposal procedures.

Storage Conditions

Advise patients that the recommended storage condition for Glatopa is refrigeration at 36°F to 46°F (2°C to 8°C). If needed, the patient may store Glatopa at room temperature, 59°F to 86°F (15°C to 30°C), for up to one month, but refrigeration is preferred. Glatopa should not be exposed to higher temperatures or intense light. Do not freeze Glatopa.

PATIENT INFORMATION

Glatopa®
(gluh-TOH-puh)
(glatiramer acetate injection) for Subcutaneous Use

Read this Patient Information before you start using Glatopa and each time you get a refill. There may be new information. This information does not take the place of talking with your doctor about your medical condition or your treatment.

What is Glatopa?

Glatopa is a prescription medicine that is used to treat relapsing forms of multiple sclerosis (MS), to include clinically isolated syndrome, relapsing-remitting disease, and active secondary progressive disease, in adults.

It is not known if Glatopa is safe and effective in children under 18 years of age.

Who should not use Glatopa?

- Do not use Glatopa if you are allergic to glatiramer acetate, mannitol or any of the ingredients in Glatopa. See the end of this leaflet for a complete list of the ingredients in Glatopa.

What should I tell my doctor before using Glatopa? Before you use Glatopa, tell your doctor if you:

- are pregnant or plan to become pregnant. It is not known if glatiramer acetate will harm your unborn baby.
- are breastfeeding or plan to breastfeed. It is not known if glatiramer acetate passes into your breast milk. Talk to your doctor about the best way to feed your baby while using Glatopa.

Tell your doctor about all the medicines you take, including prescription and over-the-counter medicines, vitamins, and herbal supplements.

Glatopa may affect the way other medicines work, and other medicines may affect how Glatopa works.

Know the medicines you take. Keep a list of your medicines with you to show your doctor and pharmacist when you get a new medicine.

How should I use Glatopa?

- For detailed instructions, see the Instructions for Use at the end of this leaflet for complete information on how to use Glatopa.
- Your doctor will tell you how much Glatopa to use and when to use it.
- Glatopa is given by injection under your skin (subcutaneously).
- Use Glatopa exactly as your doctor tells you to use it.
- Since every body type is different, talk with your doctor about the injection areas that are best for you.
- You should receive your first dose of Glatopa with a doctor or nurse present. This might be at your doctor’s office or with a visiting home health nurse who will teach you how to give your Glatopa injections.

What are the possible side effects of Glatopa?

Glatopa may cause serious side effects, including:

- Immediate Post-Injection Reactions. Serious side effects may happen right after or within minutes after you inject Glatopa at any time during your course of treatment. Call your doctor right away if you have any of these immediate post-injection reaction symptoms including:
  ∘ redness to your cheeks or other parts of the body (flushing)
  ∘ chest pain
  ∘ fast heart beat
  ∘ anxiety
  ∘ breathing problems or tightness in your throat
  ∘ swelling, rash, hives, or itching
If you have symptoms of an immediate post-injection reaction, do not give yourself more injections until a doctor tells you to.
- Chest Pain. You can have chest pain as part of an immediate post-injection reaction or by itself. This type of chest pain usually lasts a few minutes and can begin around 1 month after you start using Glatopa. Call your doctor right away if you have chest pain while using Glatopa.
- Damage to your skin. Damage to the fatty tissue just under your skin’s surface (lipoatrophy) and, rarely, death of your skin tissue (necrosis) can happen when you use Glatopa. Damage to the fatty tissue under your skin can cause a “dent” at the injection site that may not go away. You can reduce your chance of developing these problems by:
  ∘ following your doctor’s instructions for how to use Glatopa
  ∘ choosing a different injection area each time you use Glatopa. See Step 4 in the Instructions for Use, “Choose your injection area”.
- Liver problems. Liver problems, including liver failure, can occur with Glatopa. Call your healthcare provider right away if you have symptoms, such as:
○ nausea
○ loss of appetite
○ tiredness
○ dark colored urine and pale stools
○ yellowing of your skin or the white part of your eye
○ bleeding more easily than normal
○ confusion
○ sleepiness

The most common side effects of Glatopa include:

- skin problems at your injection site including:
  ∘ redness
  ∘ pain
  ∘ swelling
  ∘ itching
  ∘ lumps
- rash
- shortness of breath
- flushing (vasodilation)

Tell your doctor if you have any side effect that bothers you or that does not go away.

These are not all the possible side effects of Glatopa. For more information, ask your doctor or pharmacist.

Call your doctor for medical advice about side effects. You may report side effects to FDA at 1-800-FDA-1088.

How should I store Glatopa?

- Store Glatopa in the refrigerator between 36°F to 46°F (2°C to 8°C).
- When you are not able to refrigerate Glatopa, you may store it for up to 1 month at room temperature between 59°F to 86°F (15°C to 30°C).
- Protect Glatopa from light or high temperature.
- Do not freeze Glatopa syringes. If a syringe freezes, throw it away in a sharps disposal container. See Step 13 in the Instructions for Use, “Dispose of your needles and syringes”.

Keep Glatopa and all medicines out of the reach of children.

General information about the safe and effective use of Glatopa.

Medicines are sometimes prescribed for purposes other than those listed in a Patient Information Leaflet. Do not use Glatopa for a condition for which it was not prescribed. Do not give Glatopa to other people, even if they have the same symptoms as you have. It may harm them.

This Patient Information Leaflet summarizes the most important information about Glatopa. If you would like more information, talk with your doctor. You can ask your pharmacist or doctor for information about Glatopa that is written for health professionals.

For more information, go to www.glatopa.com or call Sandoz GlatopaCare® at 1-855-452-8672.

What are the ingredients in Glatopa?

Active ingredient: glatiramer acetate

Inactive ingredients: mannitol

INSTRUCTIONS FOR USE

Glatopa®
(gluh-TOH-puh)
(glatiramer acetate injection) for Subcutaneous Use

For subcutaneous injection only.

Do not inject Glatopa in your veins (intravenously).

Do not re-use your Glatopa pre-filled syringes.

Do not share your Glatopa pre-filled syringes with another person. You may give another person an infection or get an infection from them.

You should receive your first dose of Glatopa with a doctor or nurse present. This might be at your doctor’s office or with a visiting home health nurse who will show you how to give your own injections.

Glatopa comes in either a 20 mg Pre-filled Syringe with needle attached or a 40 mg Pre-filled Syringe with needle attached. How often a dose is given depends on the product strength that is prescribed. Your doctor will prescribe the correct dose for you.

Instructions for Using Your Glatopa 20 mg Pre-filled Syringe:

- Glatopa 20 mg is injected 1 time each day, in the fatty layer under your skin (subcutaneously).
- Each Glatopa 20 mg pre-filled syringe is for single use (1 time use) only.
- The Glatopa 20 mg dose is packaged in boxes of 30 pre-filled syringes with needles attached. Glatopa 20 mg pre-filled syringes have white plungers.

Instructions for Using Your Glatopa 40 mg Pre-filled Syringe:

- Glatopa 40 mg is injected 3 times each week, in the fatty layer under your skin (subcutaneously).
- Glatopa 40 mg should be given on the same 3 days each week, if possible for example, Monday, Wednesday, and Friday. Give your Glatopa injections at least 48 hours (2 days) apart.
- Each Glatopa 40 mg pre-filled syringe is for single use (1 time use) only.
- The Glatopa 40 mg dose is packaged in boxes of 12 pre-filled syringes with needles attached. Glatopa 40 mg pre-filled syringes have blue plungers.

How do I inject Glatopa?

Step 1: Gather the supplies you will need to inject Glatopa. See Figure A.

- 1 blister pack with a Glatopa Pre-filled Syringe with needle attached
- Alcohol wipe (not supplied)
- Dry cotton ball (not supplied)
- A place to record your injections, like a notebook (not supplied)
- Sharps disposal container (not supplied). See Step 13 below, “Dispose of your needles and syringes”.

Figure A

Step 2: Remove only 1 blister pack from the Glatopa pre-filled syringe carton. See Figure B.

Figure B

- Place the supplies you will need on a clean, flat surface in a well-lit area.
- After you remove 1 blister pack from the carton, keep all unused syringes in the carton and store them in the refrigerator.
- Let the blister pack, with the syringe inside, warm to room temperature for about 20 minutes.
- Wash your hands. Be careful not to touch your face or hair after washing your hands.

Step 3: Look closely at your Glatopa pre-filled syringe.

- There may be small air bubbles in the syringe. Do not try to push the air bubble from the syringe before giving your injection so you do not lose any medicine.
- Check the liquid medicine in the syringe before you give your injection. The liquid in the syringe should look clear, and colorless, and may look slightly yellow. If the liquid is cloudy or contains any particles, do not use the syringe and throw it away in a sharps disposal container. See Step 13 below, “Dispose of your needles and syringes.”

Step 4: Choose your injection area. See Figure C.

See the injection areas you should use on your body. Talk with your doctor about the injection areas that are best for you.

- The possible injection areas on your body include (See Figure C):
  ∘ your stomach area (abdomen) around the belly button
  ∘ the back of your upper arms
  ∘ upper hips (below your waist)
  ∘ your thighs (above your knees)

Abdomen

Avoid about 2 inches around the belly button

Back of Hips and Arms

Fleshy areas of the upper hips, always below the waist

Fleshy areas of the upper back portion of the arms

Arms

Fleshy areas of the upper back portion

Thighs

About 2 inches above the knee and 2 inches below the groin

Figure C

- For each Glatopa dose, choose a different injection area from 1 of the areas shown above. See Figure C.
- Do not stick the needle in the same place (site) more than 1 time each week. Each injection area contains multiple injection sites for you to choose from. Avoid injecting in the same site over and over again.
- Keep a record of the sites where you give your injection each day so you will remember where you already injected.

Step 5: Prepare to give your injection.

- There are some injection areas on your body that are hard to reach (like the back of your arm). You may need help from someone who has been instructed on how to give your injection if you cannot reach certain injection areas.
- Do not inject in sites where the skin has scarring or “dents”. Using scarred or dented skin for your injections may make your skin worse.

Step 6: Clean your injection site.

- Clean the injection site using the alcohol wipe and allow your skin to air dry. See Figure D.

Figure D

Step 7: Pick up the syringe with 1 hand and hold it like a pencil. Remove the needle cover with your other hand and set it aside. See Figure E.

Figure E

Step 8: Pinch about a 2 inch fold of skin between your thumb and index finger. See Figure F.

Figure F

Step 9: Giving your injection.

- Rest the heel of your hand holding the syringe against your skin at the injection site. Insert the needle at a 90 degree angle straight into your skin. See Figure G.

Figure G

- When the needle is all the way into your skin, release the fold of skin. See Figure H.

Figure H

Step 10: Give your Glatopa injection.

To inject the medicine, hold the syringe steady and slowly push down the plunger. See Figure I.

Figure I

Step 11: Remove the needle.

After you have injected all of the medicine, pull the needle straight out. See Figure J.

Figure J

Step 12: Use a clean, dry cotton ball to gently press on the injection site for a few seconds. Do not rub the injection site or re-use the needle or syringe. See Figure K.

Figure K

Step 13: Dispose of your needles and syringes.

- Put your used needles and syringes in a FDA-cleared sharps disposal container right away after use. Do not throw away (dispose of) loose needles and syringes in your household trash.
- If you do not have a FDA-cleared sharps disposal container, you may use a household container that is:
  ∘ made of a heavy-duty plastic,
  ∘ can be closed with a tight-fitting, puncture-resistant lid, without sharps being able to come out,
  ∘ upright and stable during use,
  ∘ leak-resistant, and
  ∘ properly labeled to warn of hazardous waste inside the container.
- When your sharps disposal container is almost full, you will need to follow your community guidelines for the right way to dispose of your sharps disposal container. There may be state or local laws about how you should throw away used needles and syringes. For more information about safe sharps disposal, and for specific information about sharps disposal in the state that you live in, go to the FDA’s website at: http://www.fda.gov/safesharpsdisposal.
- Do not dispose of your used sharps disposal container in your household trash unless your community guidelines permit this. Do not recycle your used sharps disposal container.

Figure L

This Patient Information and Instructions for Use has been approved by the U.S. Food and Drug Administration.

Glatopa® and GlatopaCare® are registered trademarks of Novartis AG.

Rev. July 2020

Distributed by

Sandoz Inc.

Princeton, NJ 08540

PACKAGE LABEL

Glatiramer Acetate Injection Solution #12